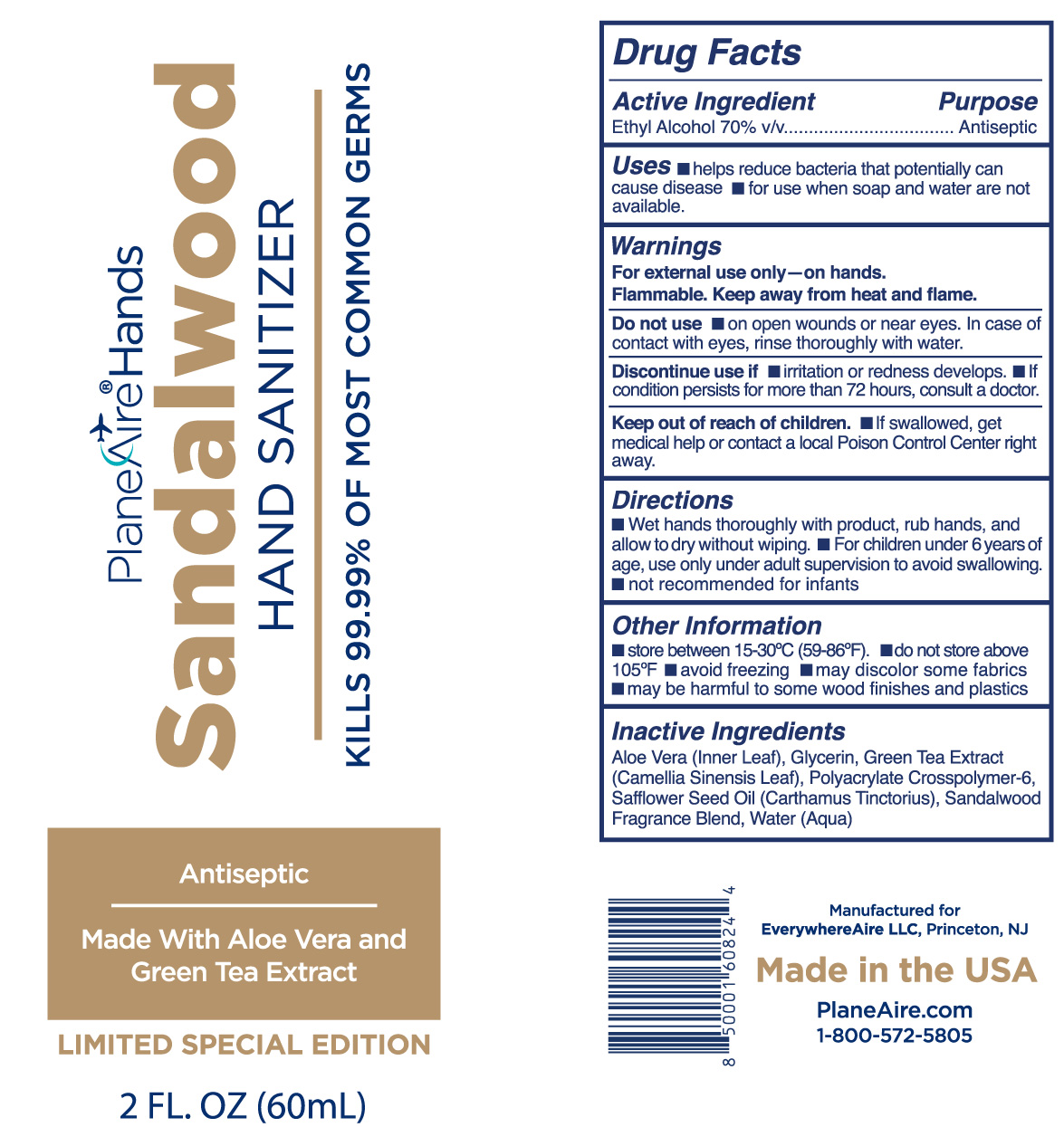 DRUG LABEL: PlaneAire Hands Sandalwood
NDC: 80335-118 | Form: LOTION
Manufacturer: EverywhereAire LLC
Category: otc | Type: HUMAN OTC DRUG LABEL
Date: 20240512

ACTIVE INGREDIENTS: ALCOHOL 70 mL/100 mL
INACTIVE INGREDIENTS: AMMONIUM ACRYLOYLDIMETHYLTAURATE, DIMETHYLACRYLAMIDE, LAURYL METHACRYLATE AND LAURETH-4 METHACRYLATE COPOLYMER, TRIMETHYLOLPROPANE TRIACRYLATE CROSSLINKED (45000 MPA.S); SAFFLOWER OIL; SANDALWOOD OIL; WATER; GLYCERIN; GREEN TEA LEAF

PlaneAire Hands Sandalwood lotion hand sanitizer

Acttive Ingredient(s)

Ethyl alcohol 70% v/v

Purpose

Topical antiseptic

Use

Hand Santizer to help reduce bacteria that potentially reduce disease. For us when soap and water are not available.

Warnings

For external use only. Flammable. Keep away from heat or flame.

Do not use on open wounds or near eyes. In case of contact with eyes, rinse thoroughly with water

When using

When using this product keep out of eyes. In case of contact with eyes, rinse eyes thoroughly with water.
Stop use if irritation or rash occurs. If condition persists for more than 72 hours, consult a doctor.
Keep out of reach of children. If swallowed, get medical help or contact a local Poison Control Center right away.

Stop Use

Stop use and ask a doctor if irritation or rash occurs. These may be signs of a serious condition.

Keep out of reach of children. If swallowed, get medical help or contact a Poison Control Center right away.

Directions

- Wet hands thoroughly with product, rub hands, and allow to dry without wiping.
- For children under 6 years of age, use only under adult supervision to avoid swallowing
- Not recommended for infants

Storage and Handling

- Store between 15-30C (59-86F)
- Do not store above 105F
- Avoid freezing
- may discolor some fabrics
- may be harmful to some wood finishes and plastics

Inactive Ingredients

aloe vera, glycerin, green tea extract, polyacrylate crosspolymer-6, safflower seed oil, sandalwood fragrance blend

Package label

NDC 80335-118